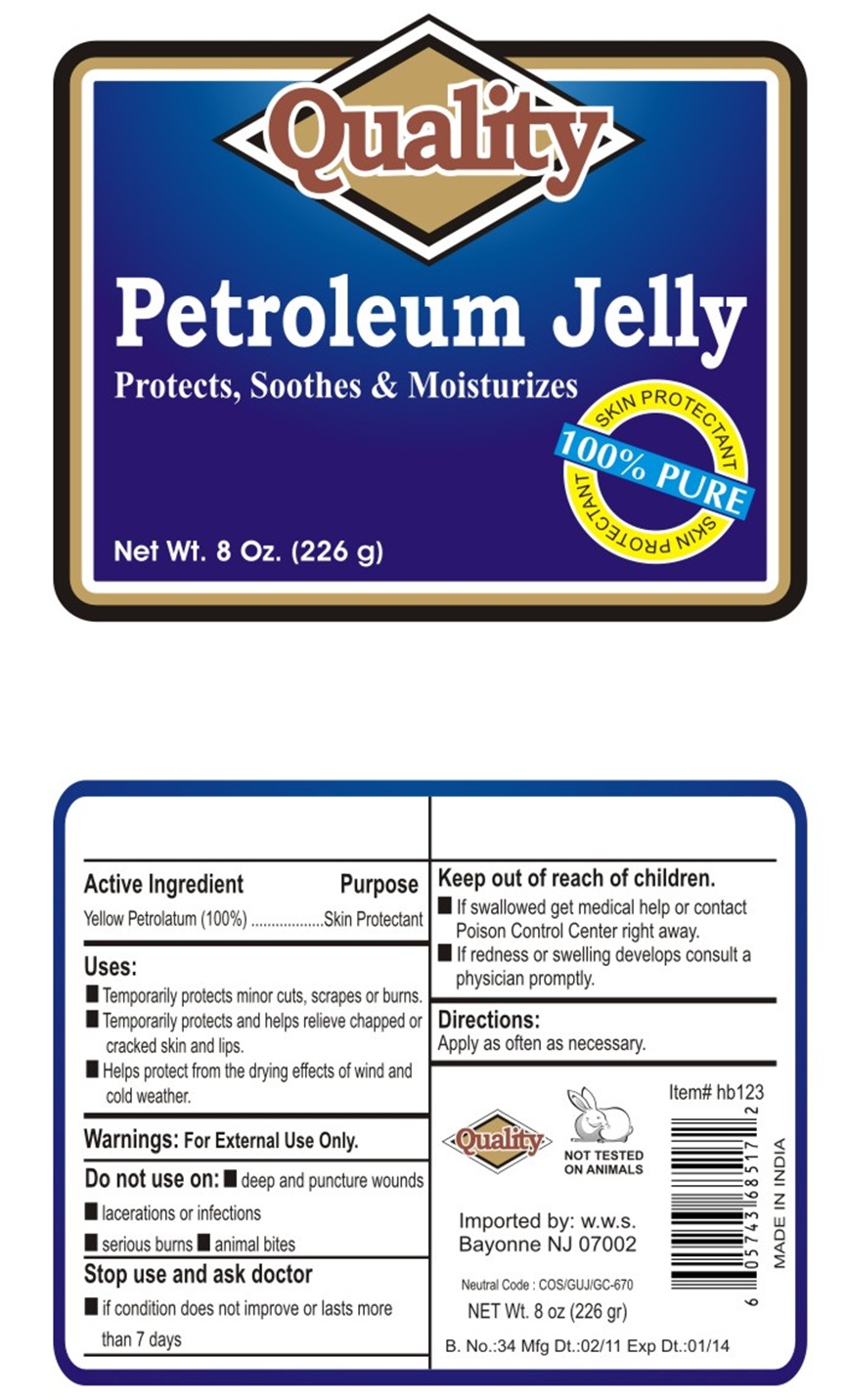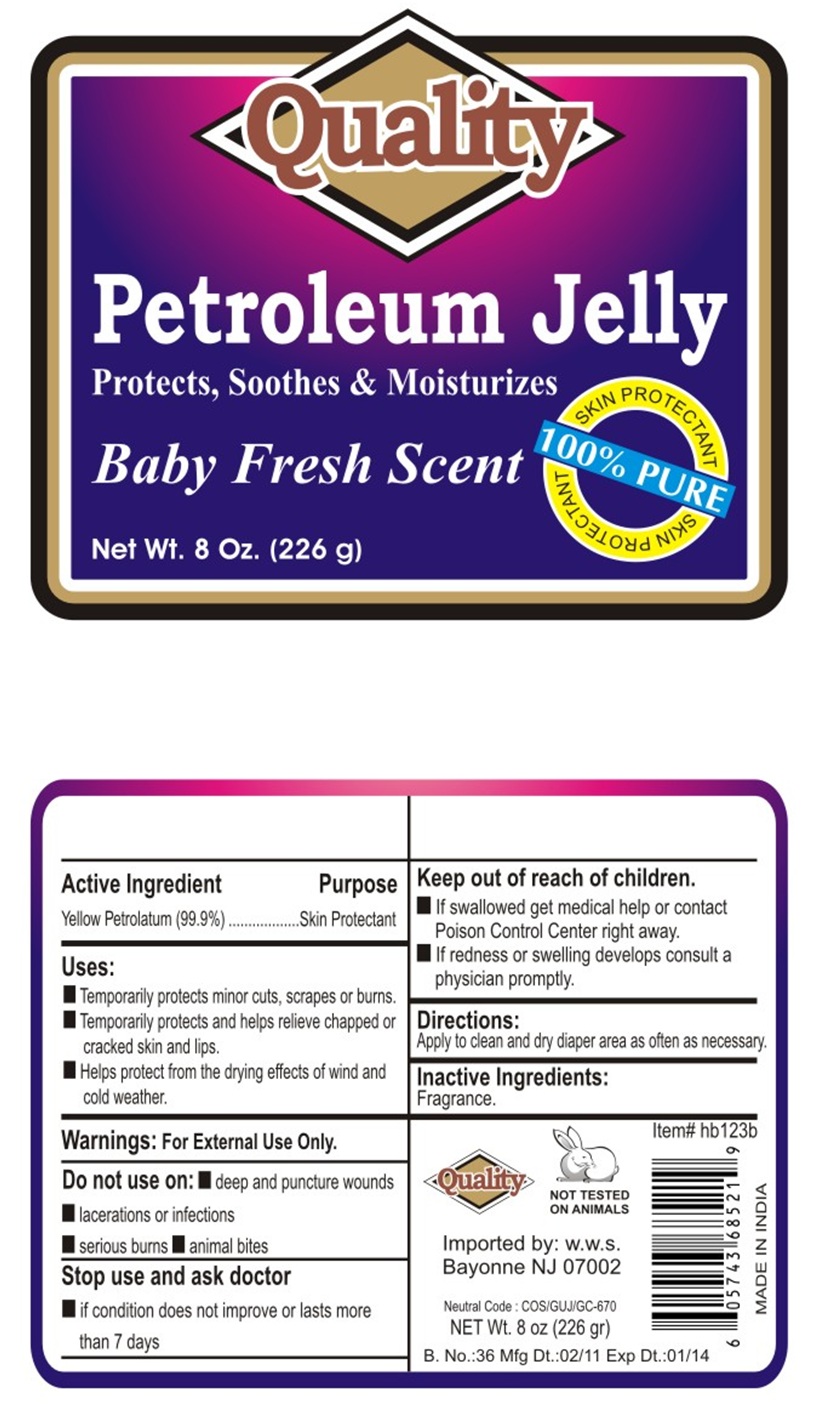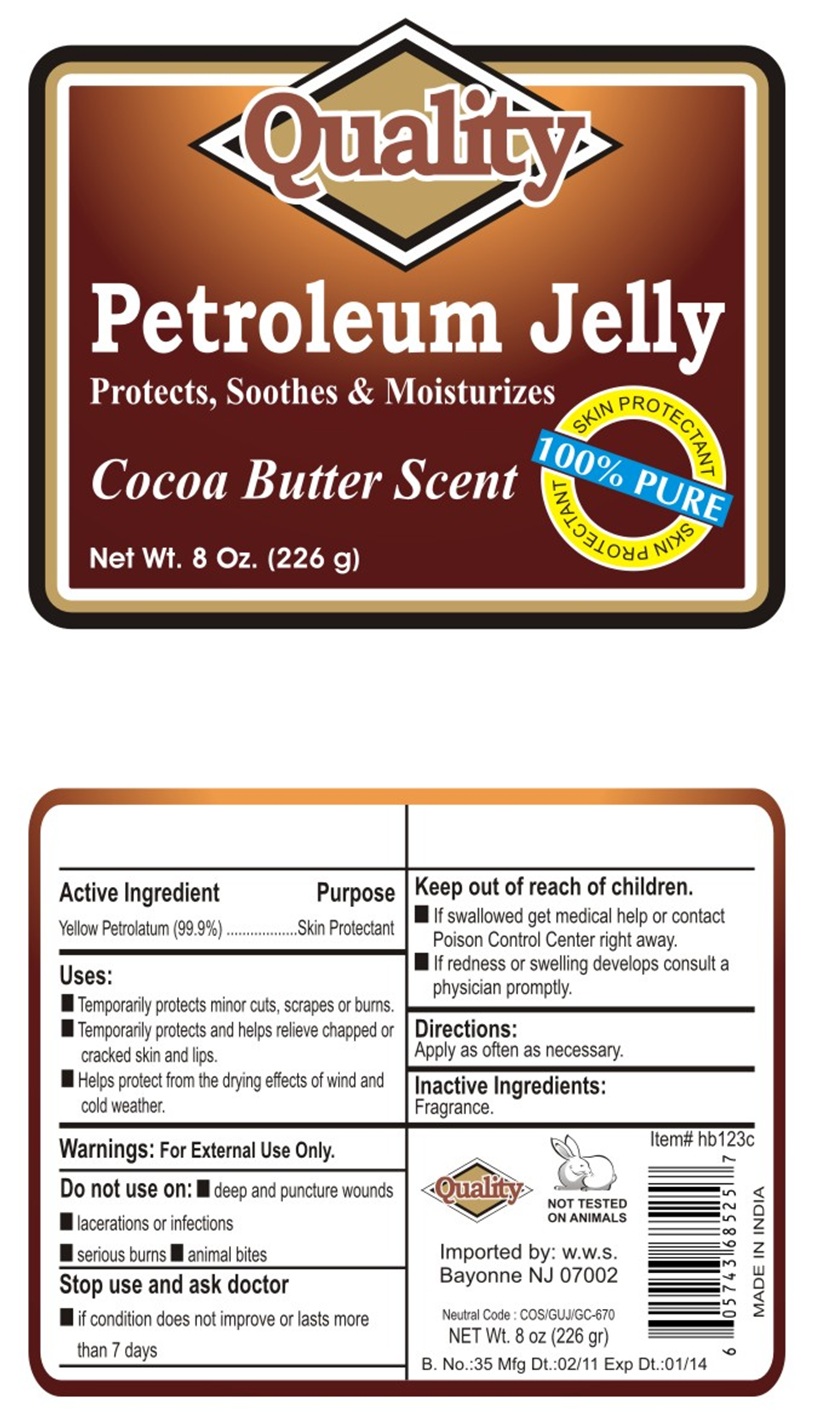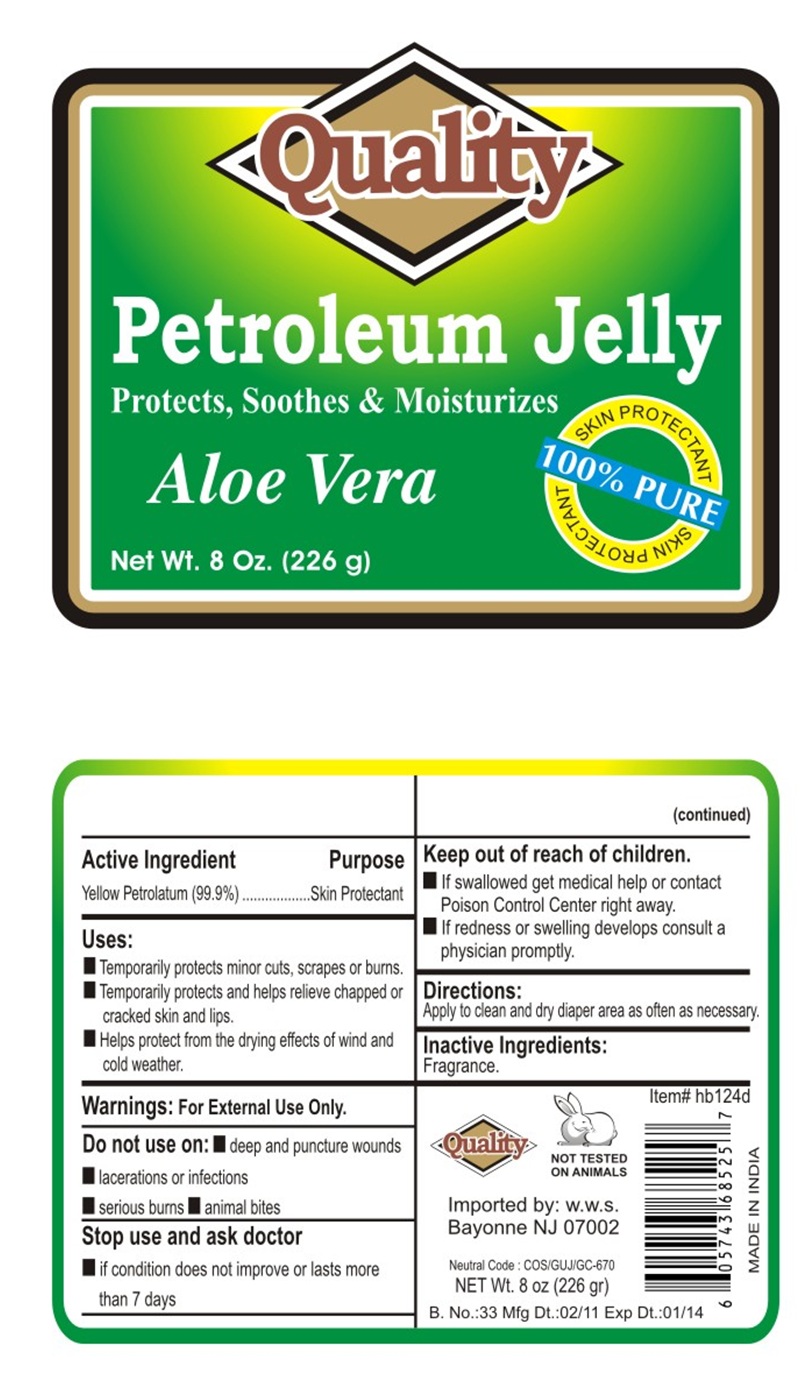 DRUG LABEL: Quality Petroleum Jelly
NDC: 76384-001 | Form: JELLY
Manufacturer: Worldwide Sales & Distribution Corp.
Category: otc | Type: HUMAN OTC DRUG LABEL
Date: 20110815

ACTIVE INGREDIENTS: PETROLATUM 1 g/1 g

Petroleum Jelly

Drug Facts

Active Ingredient

Yellow petroleum (100%)

Purpose

Skin protectant

Uses:

- Temporarily protects minor cuts, scrapes, or burns.
- Temporarily protects and helps relieve chapped or cracked skin and lips.
- Helps protect from the drying effects of wind and cold weather.

Warnings:

For External Use Only.

Do not use on:

- deep and puncture wounds
- lacerations or infections
- serious burns
- animal bites

Stop use and ask doctor

- If conditions does not improve or lasts more than 7 days

Keep out of reach of children.

- If swallowed get medical help or contact poison control center right away.
- If redness or swelling develops consult a physician promptly.

Directions:

- Apply as often as necessary.

Inactive Ingredients:

Fragrance.

PRINCIPAL DISPLAY PANEL

Quality
Petroleum Jelly
Protects, Soothes & Moisturizes
Net Wt. 8 Oz. (226 g)

PRINCIPAL DISPLAY PANEL

Quality
Petroleum Jelly
Protects, Soothes & Moisturizes
Baby Fresh Scent
Net Wt. 8 Oz. (226 g)

PRINCIPAL DISPLAY PANEL

Quality
Petroleum Jelly
Protects, Soothes & Moisturizes
Cocoa Butter Scent
Net Wt. 8 Oz. (226 g)

PRINCIPAL DISPLAY PANEL

Quality
Petroleum Jelly
Protects, Soothes & Moisturizes
Aloe Vera
Net Wt. 8 Oz. (226 g)